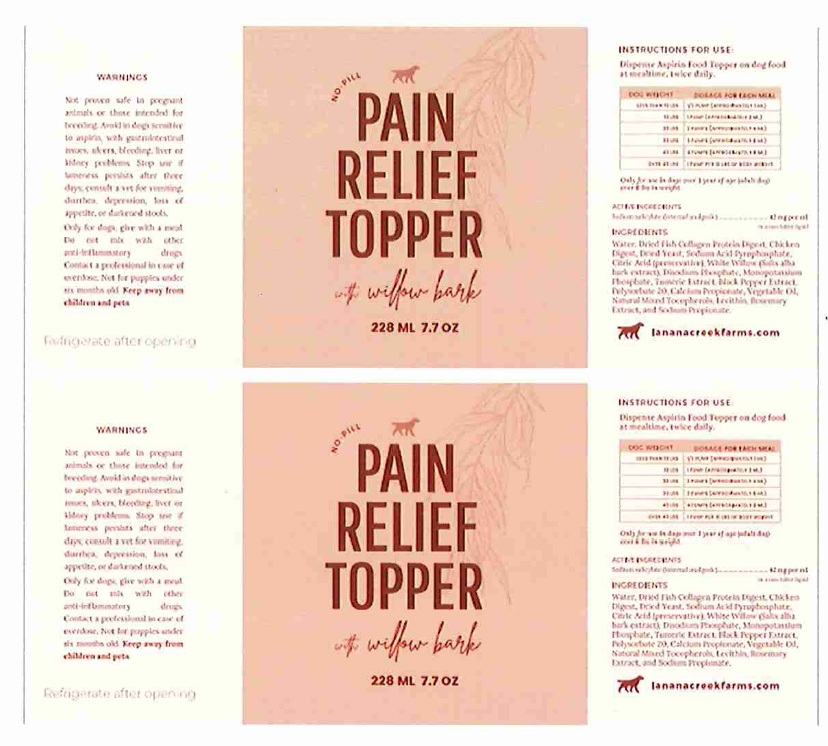 DRUG LABEL: Lanana Creek Farms Pain Relief Topper
NDC: 57932-007 | Form: LIQUID
Manufacturer: Animal Science Products, Inc.
Category: animal | Type: OTC ANIMAL DRUG LABEL
Date: 20250414

ACTIVE INGREDIENTS: SODIUM SALICYLATE 42 mg/1 mL
INACTIVE INGREDIENTS: MARINE COLLAGEN, SOLUBLE; CHICKEN; SACCHAROMYCES CEREVISIAE; SODIUM ACID PYROPHOSPHATE; CITRIC ACID MONOHYDRATE; SALIX ALBA BARK; SODIUM PHOSPHATE, DIBASIC, ANHYDROUS; MONOBASIC POTASSIUM PHOSPHATE; TURMERIC; BLACK PEPPER; POLYSORBATE 20; CALCIUM PROPIONATE; CORN OIL; TOCOPHEROL; SOYBEAN LECITHIN; ROSEMARY; SODIUM PROPIONATE

Active Ingredient

Sodium Salicylate (internal analgesic) ..........................42mg per ml. in a non-tablet liquid

Purpose

To relieve pain, reduce inflammation, and lower fever

Uses

Dogs Greater 1 Year of Age and over 6lbs

Warnings

Not proven safe in pregnant animals or those intended for breeding. Avoid in dogs sensitive to aspirin, with gastrointestinal issues, ulcers, bleeding liver or kidney problems. Stop usc if lameness persists after 3 days: consult Vet for vomiting, diarrhea, depression, loss of appetite, or darkened stools. ONLY FOR DOGS; GIVE WITH A MEAL. Do not mix with other anti-inflammatory drugs. Contact professional in case of overdose. Not for puppies under six months old. Keep away from children and pets.

Directions

Dispense Aspirin Food Topper on dog food twice daily.
Refer to dosage chart based on dog's weight on label.

DOG WEIGHT | DOSAGE FOR EACH MEAL
LESS THAN 10 LBS | 1/2 PUMP (APPROXIMATELY 1ML)
10 LBS | 1 PUMP (APPROXIMATELY 2 ML)
20 LBS | 2 PUMP (APPROXIMATELY 4 ML)
30 LBS | 3 PUMP (APPROXIMATELY 6 ML)
40 LBS | 4 PUMP (APPROXIMATELY 8 ML)
Over 40 LBS | 1 PUMP PER 10 LBS OF BODY WEIGHT

Inactive Ingredients

Water, Dried fish collagen protein digest, chicken digest, dried yeast, sodium acid pyrophosphate, citric acid, white willow, disodium phosphate, monopotassium phosphate, turmeric extract, black pepper extract, polysorbate 20,calcium propionate, vegetable oil, natural mixed tocopherols, lecithin, Rosemary extract, and sodium propionate.